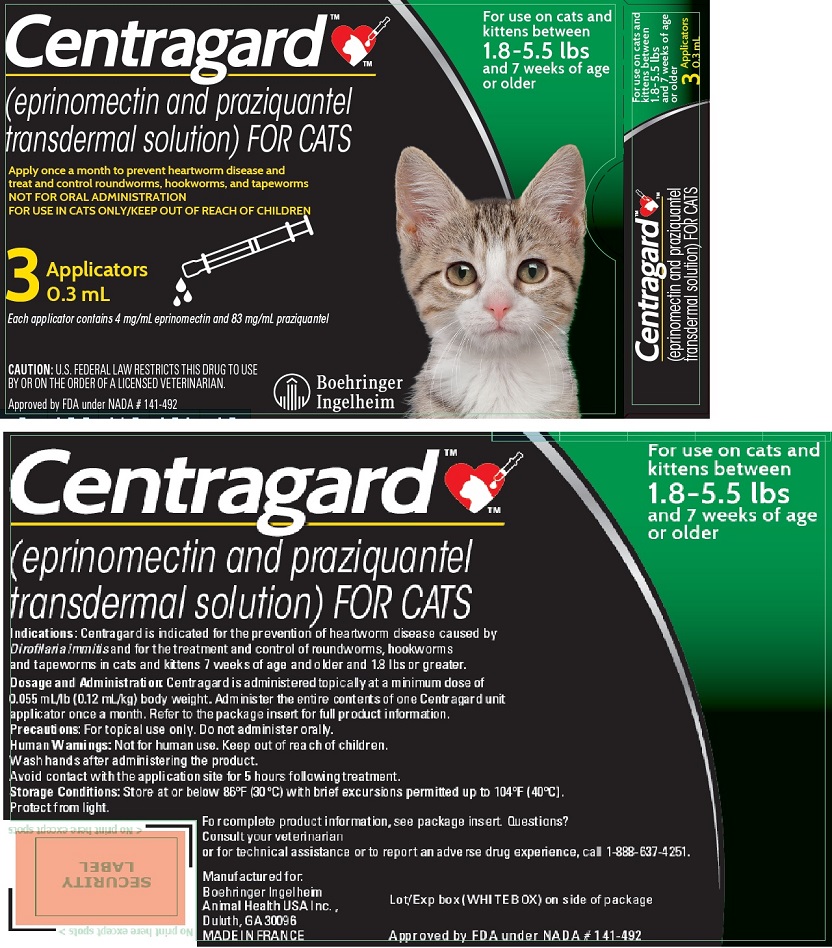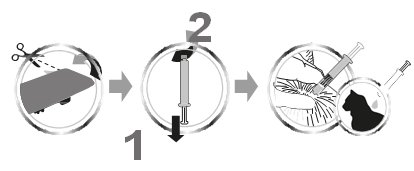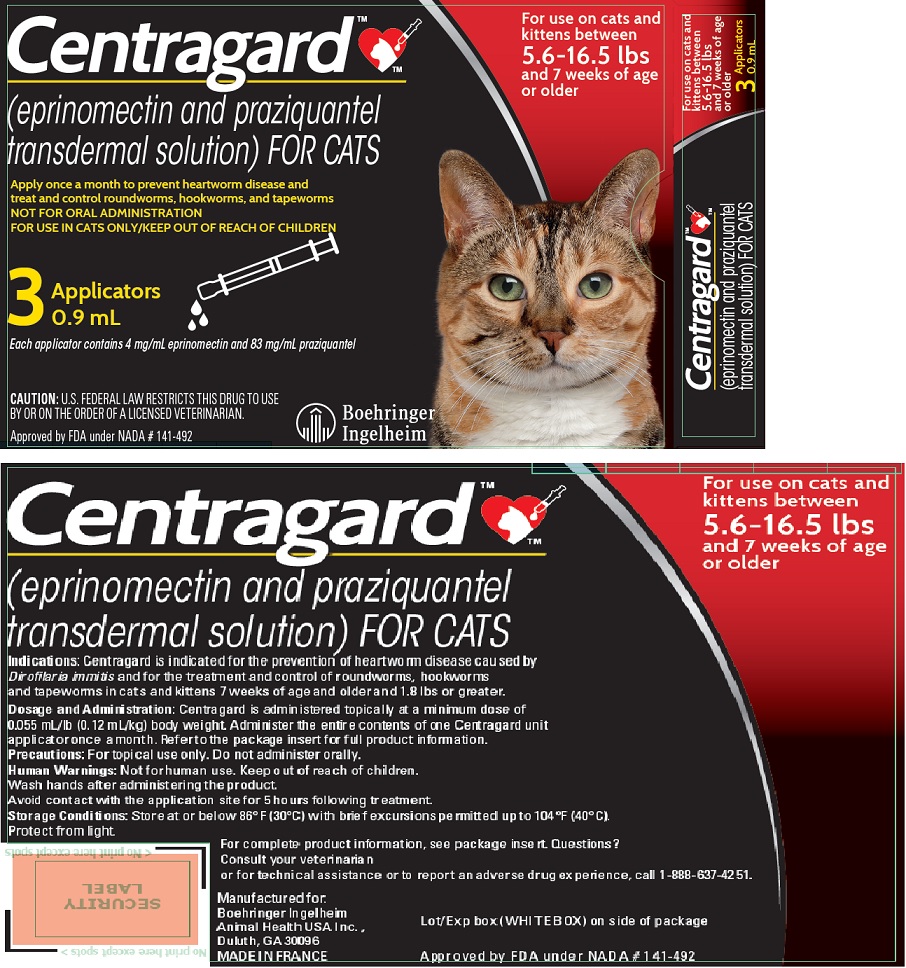 DRUG LABEL: Centragard
NDC: 0010-4243 | Form: SOLUTION
Manufacturer: Boehringer Ingelheim Animal Health USA Inc.
Category: animal | Type: PRESCRIPTION ANIMAL DRUG LABEL
Date: 20241216

ACTIVE INGREDIENTS: EPRINOMECTIN 4 mg/1 mL; PRAZIQUANTEL 83 mg/1 mL

Centragard™
(eprinomectin and praziquantel transdermal solution)
FOR CATS

CAUTION

Federal (USA) law restricts this drug to use by or on the order of a licensed veterinarian.

DESCRIPTION

CENTRAGARD is a transdermal solution containing eprinomectin and praziquantel available in 0.3 mL and 0.9 mL unit applicators to treat cats from 1.8 lbs to 33 lbs. Each mL of CENTRAGARD contains 4 mg of eprinomectin and 83 mg of praziquantel, as well as the inactive ingredients (dimethyl isosorbide, glycerol formal, and butylated hydroxytoluene). Eprinomectin belongs to the avermectin class of anthelmintics and is a mixture of homologous components referred to as eprinomectin B1a and B1b. Praziquantel is a pyrazinoisoquinoline anthelmintic.

INDICATIONS

CENTRAGARD is indicated for the prevention of heartworm disease caused by Dirofilaria immitis, and for the treatment and control of roundworms (adult and fourth stage larval Toxocara cati), hookworms (adult and fourth stage larval Ancylostoma tubaeforme; adult Ancylostoma braziliense), and tapeworms (adult Dipylidium caninum and Echinococcus multilocularis) in cats and kittens 7 weeks of age and older and 1.8 lbs or greater.

DOSAGE AND ADMINISTRATION

CENTRAGARD is dosed at a minimum of 0.055 mL/lb (0.12 mL/kg), which delivers a minimum dose of 0.23 mg/lb eprinomectin and 4.55 mg/lb praziquantel. Administer the entire contents of a CENTRAGARD unit applicator topically once a month as specified in the following table:

Cat Weight (lb) | Volume (mL) | Eprinomectin (mg) | Praziquantel (mg)
1.8-5.5 | 0.3 | 1.2 | 24.9
5.6-16.5 | 0.9 | 3.6 | 74.7
16.6-22.0 | 0.3 + 0.9 | 4.8 | 99.6
22.1-33.0 | 0.9 + 0.9 | 7.2 | 149.4

To apply CENTRAGARD pull back the plunger of the unit applicator slightly and remove the cap. Part the hair in one spot on the midline of the neck between the base of the skull and the shoulder blades, place the tip of the unit applicator on the skin and apply the contents directly on the skin. If the weight of the cat requires a second application, apply the contents in the same manner as described above in the same location. Discard applicator after use.

HEARTWORM PREVENTION
For prevention of heartworm disease, CENTRAGARD should be administered once a month. CENTRAGARD may be administered year round or at a minimum, should start 1 month before the cat’s first expected exposure to mosquitoes and continuing at monthly intervals until at least one month after the cat’s last exposure to mosquitoes. If a dose is missed and a 30-day interval between doses is exceeded, administer CENTRAGARD immediately and resume the monthly dosing schedule.

When replacing another monthly heartworm preventive product in a heartworm prevention program, the first treatment with CENTRAGARD should be given within one month of the last dose of the former medication. At the discretion of the veterinarian, cats older than 6 months of age may be tested to determine the presence of existing heartworm infection before treatment with CENTRAGARD.

TREATMENT AND CONTROL OF ROUNDWORMS, HOOKWORMS AND TAPEWORMS
CENTRAGARD treats and controls roundworms (adult and fourth stage larval Toxocara cati), hookworms (adult and fourth stage larval Ancylostoma tubaeformae, adult Ancylostoma braziliense), and tapeworms (adult Dipylidium caninum and Echinococcus multilocularis) after a single administration or when given monthly as part of a heartworm prevention program. Cats may be exposed to and can become infected with roundworms, hookworms, and tapeworms throughout the year, regardless of season or climate. Clients should be advised of appropriate measures to prevent reinfection of their cat with intestinal parasites. Because the prepatent period for E. multilocularis may be as short as 26 days, cats treated at the labeled monthly intervals may become reinfected and shed eggs between treatments.

HUMAN WARNING

Not for human use. Keep out of reach of children. Avoid contact with the application site for 5 hours following treatment. Wash hands after administering the product. If the product accidentally gets into the eyes, flush thoroughly with water. In case of accidental ingestion, or if skin or eye irritation occurs, contact a poison control center or physician for treatment advice.

PRECAUTIONS

Do not administer orally. Cats may salivate excessively and vomit if CENTRAGARD is accidentally administered orally or is ingested through licking/grooming the application site (see ANIMAL SAFETY).

The safety of CENTRAGARD has not been tested in breeding, pregnant or lactating cats.

The safety of CENTRAGARD has not been tested in kittens less than 7-9 weeks of age or weighing less than 1.8 lbs (0.8 kg).

ADVERSE REACTIONS

In a well-controlled field study, emesis, anorexia, lethargy, temporary clumping or spiking of the hair, or mild, transient skin reactions (itching, hair loss) were reported. When cats licked the application site after treatment, temporary excessive salivation was observed. Oral ingestion of CENTRAGARD may also result in hypersalivation, vomiting and/or lethargy. In margin of safety studies, transient neurological signs such as ataxia, disorientation, lethargy, and pupil dilation were observed in some cats. Correct application will minimize the occurrence of such events.

To report suspected adverse events, for technical assistance or to obtain a copy of the SDS, contact Boehringer Ingelheim Animal Health USA Inc. at 1-888-637-4251.

For additional information about adverse drug experience reporting for animal drugs, contact FDA at 1-888-FDA-VETS or online at http://www.fda.gov/AnimalVeterinary/SafetyHealth.

The Safety Data Sheet (SDS) provides additional occupational safety information. For customer service or to obtain product information, including the SDS, call 1-888-637-4251.

INFORMATION FOR OWNER OR PERSON TREATING ANIMAL

Echinococcus multilocularis is a tapeworm found in wild canids and domestic cats. E. multilocularis can infect humans and cause serious disease (alveolar hydatid disease). Owners of cats living in areas where E. multilocularis are endemic should be instructed on how to minimize their risk of exposure to this parasite, as well as their cat's risk of exposure. Although ML-635 was 100% effective in laboratory studies in cats against E. multilocularis, no studies have been conducted to show that the use of this product will decrease the incidence of alveolar hydatid disease in humans. Because the prepatent period for E. multilocularis may be as short as 26 days, cats treated at the labeled monthly intervals may become reinfected and shed eggs between treatments.

MODE OF ACTION

Eprinomectin binds to glutamate gated chloride channels that are present in invertebrate nerve and muscle cells and increases the permeability of the cell membrane to chloride ions that triggers hyperpolarization of the nerve or muscle cell resulting in paralysis and death of the parasite.

Praziquantel’s mode of action is not precisely known but treated tapeworms undergo muscular paralysis accompanied by a rapid influx of calcium ions and the disruption of the tegument.

EFFECTIVENESS

Effectiveness studies were conducted with an early formulation (ML-635), containing 8.3% fipronil, 0.4% eprinomectin, 8.3% praziquantel, and 10% (S)-methoprene. The doses of eprinomectin and praziquantel in ML-635 are equivalent to the final formulation of CENTRAGARD (eprinomectin and praziquantel transdermal solution).

Heartworm Disease Prevention
In well-controlled laboratory studies, ML-635 provided 100% effectiveness against induced heartworm infections after a single application.

Treatment and Control of Roundworms, Hookworms, and Tapeworms
In well-controlled laboratory studies, ML-635 provided > 90% effectiveness against natural and/or induced roundworm (adult and fourth stage larval Toxocara cati); hookworm (adult and fourth stage larval Ancylostoma tubaeforme; adult Ancylostoma braziliense), and adult tapeworm (Dipylidium caninum; Echinococcus multilocularis) infections.

ANIMAL SAFETY

Margin of Safety Study: A combination of fipronil, eprinomectin, praziquantel, and (S)-methoprene was applied topically to 7 to 9 week old healthy kittens at 1, 3, or 5X the maximum dose (8 cats/group) six times at 28 day intervals. One 5X kitten exhibited ataxia, disorientation, and lethargy for 12 hours and exhibited pupil dilation for 24 hours following the 3rd treatment. This 5X kitten exhibited ataxia, disorientation, and lethargy for 6 hours, and moderate pupil dilation for 24 hours following the 4th treatment, and had pupil dilation following the 5th treatment. Hypersalivation was observed for one hour for one 5X kitten following the 1st treatment and one 3X kitten following the 4th treatment. One 5X kitten had slow pupillary light responses for one day after one treatment and one 3X kitten had slow pupillary light responses for 3 hours after one treatment. One control cat had marked pupil dilation and slow pupillary light responses lasting two hours after one treatment. Immediately post-treatment cats in all groups scratched and groomed the application site.

Study in Heartworm Positive Cats: Three groups (0X, 1X and 3X) of 12 young, adult cats, 4.7 to 6.6 months of age, were experimentally infected with adult heartworms (D. immitis) by venous transplantation. All cats were negative for heartworm antibody, antigen and microfilariae prior to transplantation. Two weeks after transplantation, immunoserology verified positive antigen and the presence of microfilaria in all enrolled cats. A combination of fipronil, eprinomectin, praziquantel, and (S)-methoprene was applied topically to cats at 1X or 3X the maximum exposure dose once every 28 days for three consecutive treatments. One cat in the 1X group exhibited cyanotic mucous membranes and tachypnea for 24 hours following the first treatment. The cat recovered and exhibited no abnormal signs following two subsequent treatments. There was no difference between the treatment groups in the number of adult D. immitis recovered at the end of the study.

Oral Administration Study: Oral tolerance was evaluated to assess the effects of accidental oral ingestion. Sixteen cats (8 male and 8 female) ranging in age from 9 - 10 months were studied. Eight cats were orally administered a combination of fipronil, eprinomectin, praziquantel, and (S)-methoprene at 1X the maximum exposure dose; the 8 control cats were sham dosed. All 8 treated cats immediately exhibited hypersalivation after oral administration, and 2 cats vomited and 3 cats were lethargic during the 1-2 hour post-treatment observations. Treated cats continued to hypersalivate and lick lips/mouth for 1-2 hours after oral administration. Cats were monitored for 14 days thereafter, during which one treated cat vomited on Day 12.

STORAGE

Store at or below 30°C (86°F) with excursions permitted to 40°C (104°F). Protect from light.

HOW SUPPLIED

CENTRAGARD is packaged as a single dose in 0.3 mL (for cats 1.8 – 5.5 lb) and 0.9 mL (for cats 5.6-16.5 lb) applicators.

Each size applicator is available in cartons containing 1, 3 or 6 applications.

Approved by FDA under NADA # 141-492

Manufactured for:

Boehringer Ingelheim Animal Health USA Inc.
Duluth, GA 30096
Made in France

CENTRAGARD™ is a trademark of Boehringer Ingelheim Animal Health USA Inc.

© 2019 Boehringer Ingeheim Animal Health USA Inc. All rights reserved.

Revision date: Dec 2018

PRINCIPAL DISPLAY PANEL – 3 x 0.3 mL DISPLAY CARTON

Centragard™

(eprinomectin and praziquantel transdermal solution) FOR CATS

Apply once a month to prevent heartworm disease and treat and control roundworms, hookworms, and tapeworms

For use on cats and kittens between 1.8 – 5.5 lbs and 7 weeks of age or older

NOT FOR ORAL ADMINISTRATION

FOR USE IN CATS ONLY / KEEP OUT OF REACH OF CHILDREN

3 Applicators 0.3 mL

Each applicator contains 4 mg/mL eprinomectin and 83 mg/mL praziquantel

CAUTION: U.S. FEDERAL LAW RESTRICTS THIS DRUG TO USE BY OR ON THE ORDER OF A LICENSED VETERINARIAN.

Approved by FDA under NADA # 141-492

Boehringer Ingelheim

PRINCIPAL DISPLAY PANEL – 3 x 0.9 mL DISPLAY CARTON

Centragard™

(eprinomectin and praziquantel transdermal solution) FOR CATS

Apply once a month to prevent heartworm disease and treat and control roundworms, hookworms, and tapeworms

For use on cats and kittens between 5.6 – 16.5 lbs and 7 weeks of age or older

NOT FOR ORAL ADMINISTRATION

FOR USE IN CATS ONLY / KEEP OUT OF REACH OF CHILDREN

3 Applicators 0.9 mL

Each applicator contains 4 mg/mL eprinomectin and 83 mg/mL praziquantel

CAUTION: U.S. FEDERAL LAW RESTRICTS THIS DRUG TO USE BY OR ON THE ORDER OF A LICENSED VETERINARIAN.

Approved by FDA under NADA # 141-492

Boehringer Ingelheim